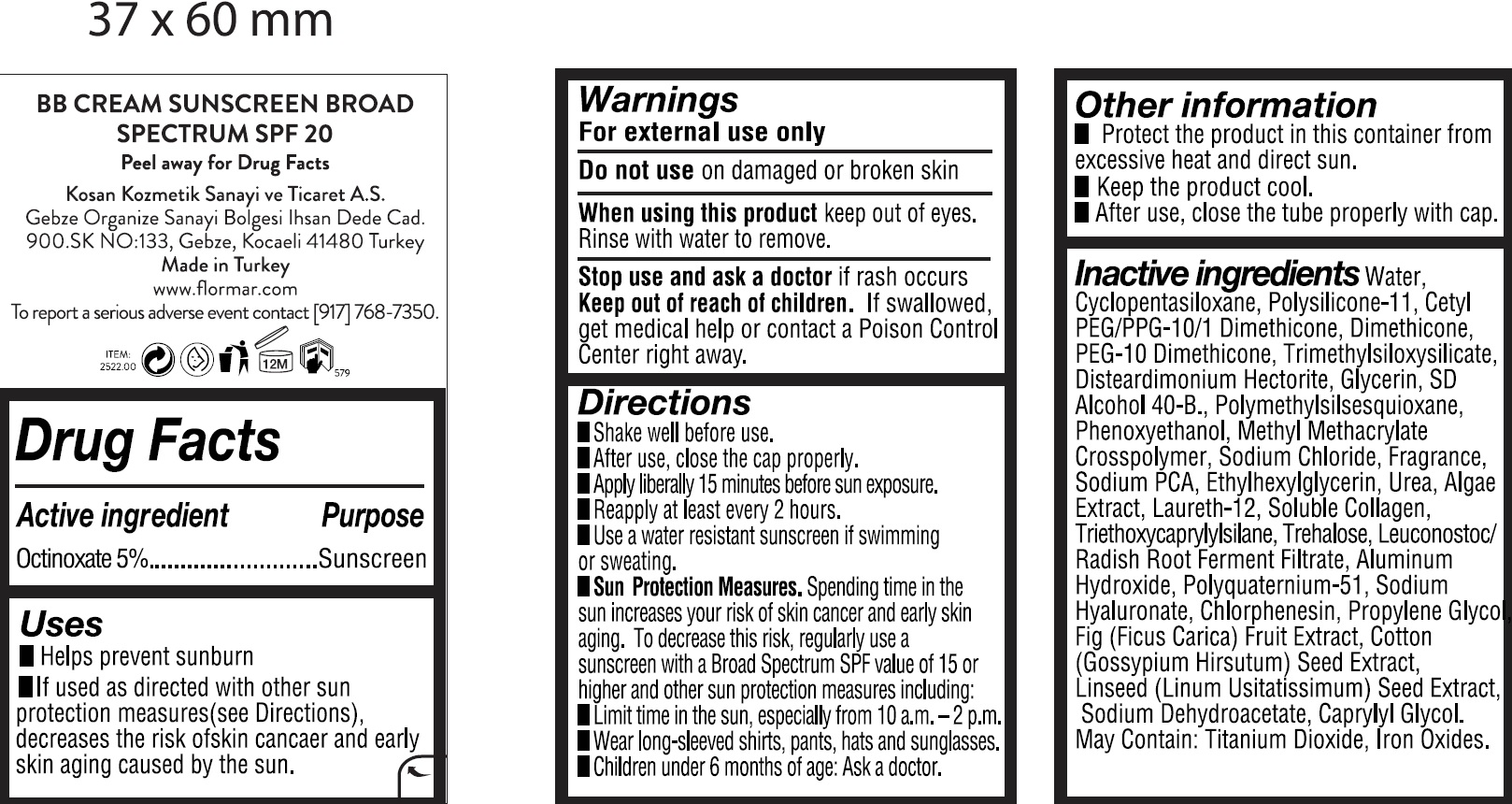 DRUG LABEL: Flormar BB BB05 Medium
NDC: 61722-360 | Form: CREAM
Manufacturer: Kosan Kozmetik Sanayi ve Ticaret Anonim Sirketi
Category: otc | Type: HUMAN OTC DRUG LABEL
Date: 20200128

ACTIVE INGREDIENTS: OCTINOXATE 50 mg/1 mL
INACTIVE INGREDIENTS: WATER; CYCLOMETHICONE 5; DIMETHICONE; PEG-10 DIMETHICONE (600 CST); TRIMETHYLSILOXYSILICATE (M/Q 0.6-0.8); DISTEARDIMONIUM HECTORITE; GLYCERIN; POLYMETHYLSILSESQUIOXANE (4.5 MICRONS); PHENOXYETHANOL; METHYL METHACRYLATE/GLYCOL DIMETHACRYLATE CROSSPOLYMER; SODIUM CHLORIDE; SODIUM PYRROLIDONE CARBOXYLATE; ETHYLHEXYLGLYCERIN; UREA; LAURETH-12; TRIETHOXYCAPRYLYLSILANE; TREHALOSE; LEUCONOSTOC/RADISH ROOT FERMENT FILTRATE; ALUMINUM HYDROXIDE; HYALURONATE SODIUM; CHLORPHENESIN; PROPYLENE GLYCOL; SODIUM DEHYDROACETATE; CAPRYLYL GLYCOL

Flormar BB Cream BB05 Medium

Active ingredient

Octinoxate 5%

Purpose

Sunscreen

Uses

- Helps prevent sunburn
- If used as directed with other sun protection measures(see Directions), decreases the risk of skin cancer and early skin aging caused by the sun.

Warnings

For external use only

Do not use

on damaged or broken skin

When using this product

keep out of eyes. Rinse with water to remove.

Stop use and ask a doctor

if rash occurs

Keep out of reach of children.

If swallowed, get medical help or contact a Posion Control Center right away.

Directions

- Shake well before use.
- After use, close the cap properly.
- Apply liberally 15 minutes before sun exposure.
- Reapply at least every 2 hours.
- Use a water resistant sunscreen if swimming or sweating.
- Sun Protection Measures. Spending time in the sun increases your risk of skin cancer and early skin aging. To decrease this risk, regularly use a sunscreen with a Broad Spectrum SPF value of 15 or higher and other sun protection measures including:
- Limit time in the sun, especially from 10 a.m. - 2 p.m.
- Wear long-sleeved shirts, pants, hats and sunglasses.
- Children under 6 months of age: Ask a doctor.

Other information

- Protect the product in this container from excessive heat and direct sun.
- Keep the product cool.
- After use, close the tube properly with cap.

Inactive ingredients

Water, Cyclopentasiloxane, Polysililone-11, Cetyl PEG/PPG-10/1 Dimethicone, Dimethicone, PEG-10 Dimethicone, Trimethylsiloxysilicate, Disteardimonium Hectorite, Glycerin, SD Alcohol 40-B., Polymethylsilsesquioxane, Phenoxyethanol, Methyl Methacrylate Crosspolymer, Sodium Chloride, Fragrance, Sodium PCA, Ethylhexylglycerin, Urea, Algae Extract, Laureth-12, Soluble Collagen, Triethoxycaprylylsilane, Trehalose, Leuconostoc/Radish Root Ferment Filtrate, Aluminum Hydroxide, Polyquaternium-51, Sodium Hyaluronate, Chlorphenesin, Propylene Glycol, Fig (Ficus Carica) Fruit Extract, Cotton (Gossypium Hirsutum) Seed Extract, Linseed (Linum Usitatissimum) Seed Extract, Sodium Dehydroacetate, Caprylyl GLycol, May Contain: Titanium Dioxide, Iron Oxides